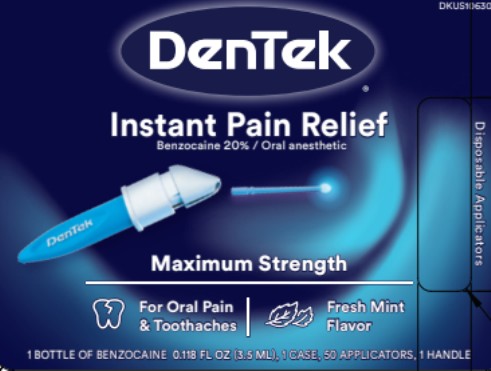 DRUG LABEL: DenTek Instant Pain Relief Maximum Strength
NDC: 60630-078 | Form: LIQUID
Manufacturer: DenTek Oral Care, Inc.
Category: otc | Type: HUMAN OTC DRUG LABEL
Date: 20250630

ACTIVE INGREDIENTS: BENZOCAINE 200 mg/1 mL
INACTIVE INGREDIENTS: PEPPERMINT OIL; POLYETHYLENE GLYCOL 400; SPEARMINT OIL; SUCRALOSE

DenTek Instant Pain Relief 60630-078-01

Drug Facts

Active ingredient

Benzocaine 20%

Purpose

Oral pain reliever

Use

for the temporary relief of pain due to:

- toothaches
- canker sores
- cold sores
- sore gums

Warnings

METHEMOGLOBINEMIA WARNING: Use of this product may cause methemoglobinemia, a serious condition that must be treated promptly because it reduces the amount of oxygen carried in blood. This can occur even if you have used this product before. Stop use and seek immediate medical attention if you or a child in your care develops:

- pale, gray, or blue colored skin (cyanosis)
- headache
- rapid heart rate
- shortness of breath
- dizziness or lightheadedness
- fatigue or lack of energy

Allergy alert: do not use this product if you have a history of allergy to local anesthetics such as procaine, butacaine, benzocaine or other “caine” anesthetics. If a skin reaction occurs, stop use and seek medical help right away.

Do not use

- for teething
- in children under 2 years of age

When using this product

- avoid contact with the eyes
- do not exceed recommended dosage
- do not use for more than 7 days unless directed by a doctor/dentist

Stop use and ask a dentist or doctor if

- swelling, rash or fever develops
- irritation, pain or redness persists or worsens
- symptoms do not improve in 7 days

Keep out of reach of children.

In case of overdose, get medical help or contact a Poison Control Center (1-800-222-1222) right away.

Directions

dip applicator into liquid

Adults and children 2 years and older | Apply a small amount of product to the affected area. Use up to 4 times daily or as directed by a dentist or doctor.
Children between 2 and 12 years | Should be supervised in the use of this product.
Children under 2 years | Do not use.

Other information

- for toothaches, use only as a temporary remedy until a dentist can be seen
- store at 20-25⁰C (68-77⁰F).

Inactive ingredients

Peppermint Oil, Polyethylene Glycol 400, Spearmint Oil, Sucralose

PRINCIPAL DISPLAY PANEL

DenTek™

INSTANT PAIN RELIEF

Benzocaine 20% / ORAL ANESTHETIC

1 BOTTLE OF BENZOCAINE 0.118 fl oz (3.5 mL), 1 CASE, 50 APPLICATORS, 1 HANDLE